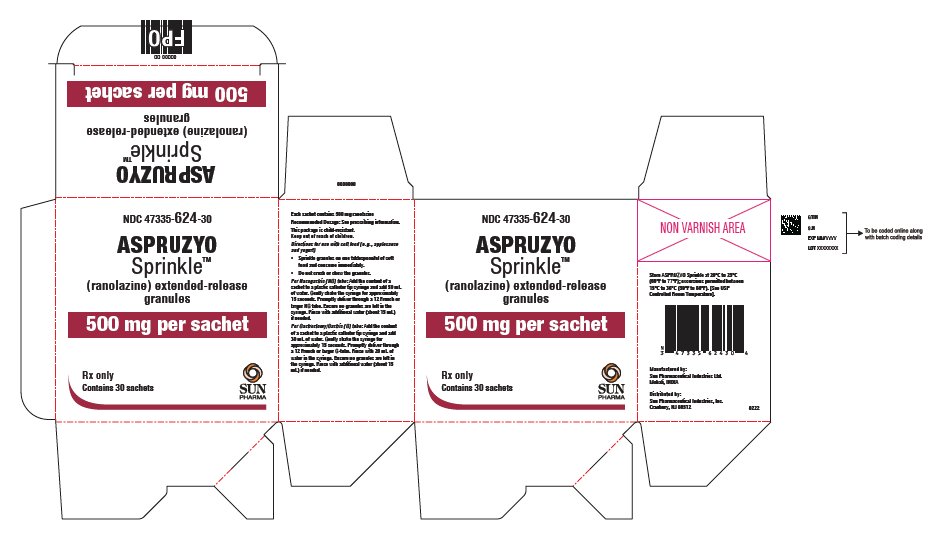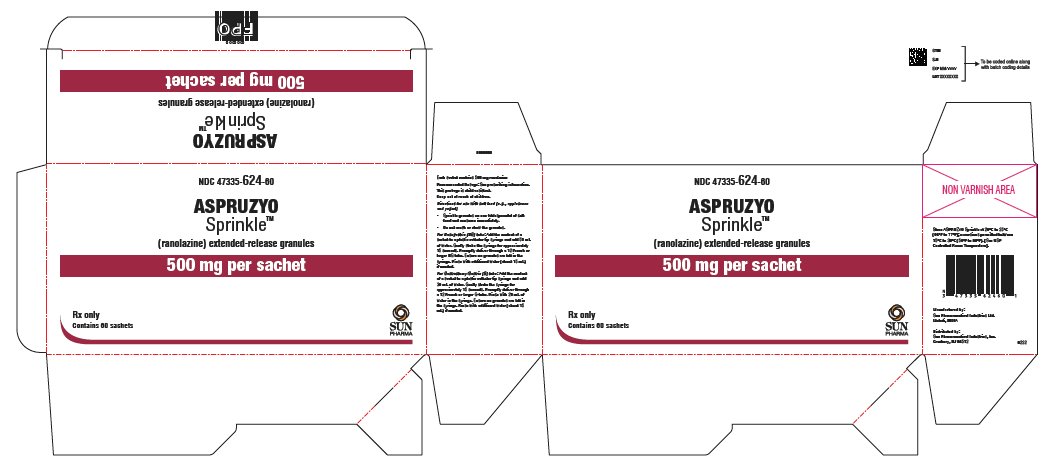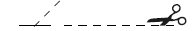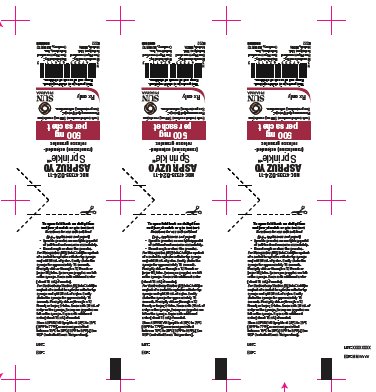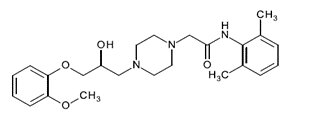 DRUG LABEL: ASPRUZYO SPRINKLE
NDC: 47335-624 | Form: GRANULE
Manufacturer: SUN PHARMACEUTICAL INDUSTRIES, INC.
Category: prescription | Type: HUMAN PRESCRIPTION DRUG LABEL
Date: 20250129

ACTIVE INGREDIENTS: RANOLAZINE 500 mg/1 1
INACTIVE INGREDIENTS: DIMETHYLAMINOETHYL METHACRYLATE - BUTYL METHACRYLATE - METHYL METHACRYLATE COPOLYMER; DIBUTYL SEBACATE; ETHYLCELLULOSE, UNSPECIFIED; HYPROMELLOSE, UNSPECIFIED; MAGNESIUM STEARATE; TALC; MICROCRYSTALLINE CELLULOSE; METHACRYLIC ACID - ETHYL ACRYLATE COPOLYMER (1:1) TYPE A

HIGHLIGHTS OF PRESCRIBING INFORMATION

These highlights do not include all the information needed to use ASPRUZYO SPRINKLE safely and effectively. See full prescribing information for ASPRUZYO SPRINKLE.
ASPRUZYO SPRINKLETM(ranolazine) extended-release granules, for oral use
Initial U.S. Approval: 2006

1 INDICATIONS AND USAGE

ASPRUZYO Sprinkle is an antianginal indicated for the treatment of chronic angina. (1)

2 DOSAGE AND ADMINISTRATION

500 mg orally twice daily and increase to 1000 mg orally twice daily, based on clinical symptoms (2.1)

3 DOSAGE FORMS AND STRENGTHS

Extended-release granules: 500 and 1000 mg (3)

4 CONTRAINDICATIONS

- Strong CYP3A inhibitors (e.g., ketoconazole, clarithromycin, nelfinavir) (4, 7.1)
- CYP3A inducers (e.g., rifampin, phenobarbital, St. John's wort) (4, 7.1)
- Liver cirrhosis (4, 8.6)

5 WARNINGS AND PRECAUTIONS

- QT interval prolongation: Can occur with ranolazine. Little information available on high doses, long exposure, use with QT interval‑ prolonging drugs, potassium channel variants causing prolonged QT interval, in patients with a family history of (or congenital) long QT syndrome, or in patients with known acquired QT interval prolongation. (5.1)
- Renal failure: Monitor renal function after initiation and periodically in patients with moderate to severe renal impairment (CrCL <60 mL/min). If acute renal failure develops, discontinue ASPRUZYO Sprinkle. (5.2)

6 ADVERSE REACTIONS

Most common adverse reactions (> 4% and more common than with placebo) are dizziness, headache, constipation, nausea. (6.1)

To report SUSPECTED ADVERSE REACTIONS, contact Sun Pharmaceutical Industries, Inc. at 1-800-818-4555 or FDA at 1-800-FDA-1088 or www.fda.gov/medwatch.

7 DRUG INTERACTIONS

- Moderate CYP3A inhibitors (e.g., diltiazem, verapamil, erythromycin): Limit ASPRUZYO Sprinkle to 500 mg twice daily. (7.1)
- P-gp inhibitors (e.g., cyclosporine): Ranolazine exposure increased. Titrate ASPRUZYO Sprinkle based on clinical response. (7.1)
- CYP3A substrates: Limit simvastatin to 20 mg when used with ASPRUZYO Sprinkle. Doses of other sensitive CYP3A substrates (e.g., lovastatin) and CYP3A substrates with narrow therapeutic range (e.g., cyclosporine, tacrolimus, sirolimus) may need to be reduced with ASPRUZYO Sprinkle. (7.2)
- OCT2 substrates: Limit the dose of metformin to 1700 mg daily when used with ASPRUZYO Sprinkle 1000 mg twice daily. Doses of other OCT2 substrates may require adjusted doses. (7.2)
- Drugs transported by P-gp (e.g., digoxin), or drugs metabolized by CYP2D6 (e.g., tricyclic antidepressants) may need reduced doses when used with ASPRUZYO Sprinkle. (7.2)

FULL PRESCRIBING INFORMATION

1 INDICATIONS AND USAGE

ASPRUZYO Sprinkle is indicated for the treatment of chronic angina.

ASPRUZYO Sprinkle may be used with beta-blockers, nitrates, calcium channel blockers, anti‑platelet therapy, lipid-lowering therapy, ACE inhibitors, and angiotensin receptor blockers.

2 DOSAGE AND ADMINISTRATION

2.1 Dosing Information

Initiate ASPRUZYO Sprinkle dosing at 500 mg orally twice daily and increase to 1000 mg orally twice daily, as needed, based on clinical symptoms.

The maximum recommended daily dose of ASPRUZYO Sprinkle is 1000 mg twice daily.

If a dose of ASPRUZYO Sprinkle is missed, take the prescribed dose at the next scheduled time; do not double the next dose.

Directions for use with soft food (e.g., applesauce and yogurt)

- Sprinkle granules on one tablespoonful of soft food and consume immediately.
- Do not crush or chew the granules.

Direction for nasogastric and gastric tube administration

Nasogastric (NG) tube:Add the content of a sachet to a plastic catheter tip syringe and add 50 mL of water. Gently shake the syringe for approximately 15 seconds. Promptly deliver through a 12 French or larger NG tube. Ensure no granules are left in the syringe. Rinse with additional water (about 15 mL) if needed.

Gastrostomy/Gastric (G) tube: Add the content of a sachet to a plastic catheter tip syringe and add 30 mL of water. Gently shake the syringe for approximately 15 seconds. Promptly deliver through a 12 French or larger G-tube. Rinse with 20 mL of water in the syringe. Ensure no granules are left in the syringe. Rinse with additional water (about 15 mL) if needed.

2.2 Dose Modification

Dose adjustments may be needed when ASPRUZYO Sprinkle is taken in combination with other drugs [see Drug Interactions (7.1)].Limit the maximum dose of ASPRUZYO Sprinkle to 500 mg twice daily in patients on moderate CYP3A inhibitors such as diltiazem, verapamil, and erythromycin. Use of ASPRUZYO Sprinkle with strong CYP3A inhibitors and CYP3A inducers is contraindicated [see Contraindications (4), Drug Interactions (7.1)].

3 DOSAGE FORMS AND STRENGTHS

ASPRUZYO Sprinkle (ranolazine) is supplied as unit-dose sachets containing 500 or 1000 mg of white to off-white, coated, extended-release granules.

4 CONTRAINDICATIONS

ASPRUZYO Sprinkle is contraindicated in patients:

- Taking strong inhibitors of CYP3A [see Drug Interactions (7.1)]
- Taking inducers of CYP3A [see Drug Interactions (7.1)]
- With liver cirrhosis [see Use in Specific Populations (8.6)]

5 WARNINGS AND PRECAUTIONS

5.1 QT Interval Prolongation

Ranolazine blocks IKrand prolongs the QTcinterval in a dose-related manner. Clinical experience in an acute coronary syndrome population did not show an increased risk of proarrhythmia or sudden death [see Clinical Studies (14.2)].However, there is little experience with high doses (> 1000 mg twice daily) or exposure, other QT‑prolonging drugs, potassium channel variants resulting in a long QT interval, in patients with a family history of (or congenital) long QT syndrome, or in patients with known acquired QT interval prolongation.

5.2 Renal Failure

Acute renal failure has been observed in patients with severe renal impairment (creatinine clearance [CrCL] < 30 mL/min) while taking ranolazine. If acute renal failure develops (e.g., marked increase in serum creatinine associated with an increase in blood urea nitrogen [BUN]), discontinue ASPRUZYO Sprinkle and treat appropriately [see Use in Specific Populations (8.7)].

Monitor renal function after initiation and periodically in patients with moderate to severe renal impairment (CrCL < 60 mL/min) for increases in serum creatinine accompanied by an increase in BUN.

6 ADVERSE REACTIONS

6.1 Clinical Trial Experience

Because clinical trials are conducted under widely varying conditions, adverse reaction rates observed in the clinical trials of a drug cannot be directly compared to rates in the clinical trials of another drug and may not reflect the rates observed in practice.

A total of 2018 patients with chronic angina were treated with ranolazine in controlled clinical trials. Of the patients treated with ranolazine, 1026 were enrolled in three double‑blind, placebo-controlled, randomized studies (CARISA, ERICA, MARISA) of up to 12 weeks' duration. In addition, upon study completion, 1251 patients received treatment with ranolazine in open-label, long-term studies; 1227 patients were exposed to ranolazine for more than 1 year, 613 patients for more than 2 years, 531 patients for more than 3 years, and 326 patients for more than 4 years.

At recommended doses, about 6% of patients discontinued treatment with ranolazine because of an adverse event in controlled studies in angina patients compared to about 3% on placebo. The most common adverse events that led to discontinuation more frequently on ranolazine than placebo were dizziness (1.3% versus 0.1%), nausea (1% versus 0%), asthenia, constipation, and headache (each about 0.5% versus 0%). Doses above 1000 mg twice daily are poorly tolerated.

In controlled clinical trials of angina patients, the most frequently reported treatment‑emergent adverse reactions (> 4% and more common on ranolazine than on placebo) were dizziness (6.2%), headache (5.5%), constipation (4.5%), and nausea (4.4%). Dizziness may be dose-related. In open-label, long-term treatment studies, a similar adverse reaction profile was observed.

The following additional adverse reactions occurred at an incidence of 0.5 to 4.0% in patients treated with ranolazine and were more frequent than the incidence observed in placebo-treated patients:

Cardiac Disorders-bradycardia, palpitations

Ear and Labyrinth Disorders-tinnitus, vertigo

Eye Disorders-blurred vision

Gastrointestinal Disorders-abdominal pain, dry mouth, vomiting, dyspepsia

General Disorders and Administrative Site Adverse Events-asthenia, peripheral edema

Metabolism and Nutrition Disorders-anorexia

Nervous System Disorders-syncope (vasovagal)

Psychiatric Disorders-confusional state

Renal and Urinary Disorders-hematuria

Respiratory, Thoracic, and Mediastinal Disorders-dyspnea

Skin and Subcutaneous Tissue Disorders-hyperhidrosis

Vascular Disorders-hypotension, orthostatic hypotension

Other (< 0.5%) but potentially medically important adverse reactions observed more frequently with ranolazine than placebo treatment in all controlled studies included: angioedema, renal failure, eosinophilia, chromaturia, blood urea increased, hypoesthesia, paresthesia, tremor, pulmonary fibrosis, thrombocytopenia, leukopenia, and pancytopenia.

A large clinical trial in acute coronary syndrome patients was unsuccessful in demonstrating a benefit for ranolazine, but there was no apparent proarrhythmic effect in these high-risk patients [see Clinical Studies (14.2)].

Laboratory Abnormalities:

Ranolazine produces elevations of serum creatinine by 0.1 mg/dL, regardless of previous renal function, likely because of inhibition of creatinine's tubular secretion. In general, the elevation has a rapid onset, shows no signs of progression during long-term therapy, is reversible after discontinuation of ranolazine, and is not accompanied by changes in BUN. In healthy volunteers, ranolazine 1000 mg twice daily had no effect upon the glomerular filtration rate. More marked and progressive increases in serum creatinine, associated with increases in BUN or potassium, indicating acute renal failure, have been reported after initiation of ranolazine in patients with severe renal impairment [see Warnings and Precautions (5.2), Use in Specific Populations (8.7)].

6.2 Post-marketing Experience

The following adverse reactions have been identified during post-approval use of ranolazine. Because these reactions are reported voluntarily from a population of uncertain size, it is not always possible to reliably estimate their frequency or establish a causal relationship to drug exposure:

Nervous System Disorders- Abnormal coordination, myoclonus, paresthesia, tremor, and other serious neurologic adverse events have been reported to occur, sometimes concurrently, in patients taking ranolazine. The onset of events was often associated with an increase in ranolazine dose or exposure. Many patients reported symptom resolution following drug discontinuation or dose decrease.

Metabolism and Nutrition Disorders- Cases of hypoglycemia have been reported in diabetic patients on antidiabetic medication.

Psychiatric Disorders- hallucination

Renal and Urinary Disorders- dysuria, urinary retention

Skin and Subcutaneous Tissue Disorders- angioedema, pruritus, rash

7 DRUG INTERACTIONS

7.1 Effects of Other Drugs on Ranolazine

Strong CYP3A Inhibitors

Concomitant use of ASPRUZYO Sprinkle with strong CYP3A inhibitors, including ketoconazole, itraconazole, clarithromycin, nefazodone, nelfinavir, ritonavir, indinavir, and saquinavir is contraindicated [see Contraindications (4), Clinical Pharmacology (12.3)].

Moderate CYP3A Inhibitors

Limit the dose of ASPRUZYO Sprinkle to 500 mg twice daily in patients on moderate CYP3A inhibitors, including diltiazem, verapamil, erythromycin, fluconazole, and grapefruit juice or grapefruit-containing products [see Dosage and Administration (2.2), Clinical Pharmacology (12.3)].

P-gp Inhibitors

Concomitant use of ASPRUZYO Sprinkle and P-gp inhibitors, such as cyclosporine, may result in increases in ranolazine concentrations. Titrate ASPRUZYO Sprinkle based on clinical response in patients concomitantly treated with predominant P-gp inhibitors such as cyclosporine [see Dosage and Administration (2.2)].

CYP3A Inducers

Concomitant use of ASPRUZYO Sprinkle with CYP3A inducers such as rifampin, rifabutin, rifapentine, phenobarbital, phenytoin, carbamazepine, and St. John's wort is contraindicated [see Contraindications (4), Clinical Pharmacology (12.3)].

Alcohol

An in-vitrodissolution study was conducted to evaluate the impact of alcohol on extended-release characteristics of ASPRUZYO Sprinkle. The in-vitrostudy showed that alcohol causes a rapid release of ranolazine from ASPRUZYO Sprinkle that may increase the risk of adverse events associated with ASPRUZYO Sprinkle. Patients should not consume alcohol when taking ASPRUZYO Sprinkle [see Clinical Pharmacology (12.3)].

7.2 Effects of Ranolazine on Other Drugs

Drugs Metabolized by CYP3A

Limit the dose of simvastatin in patients on any dose of ASPRUZYO Sprinkle to 20 mg once daily, when ASPRUZYO Sprinkle is co-administered. Dose adjustment of other sensitive CYP3A substrates (e.g., lovastatin) and CYP3A substrates with a narrow therapeutic range (e.g., cyclosporine, tacrolimus, sirolimus) may be required as ASPRUZYO Sprinkle may increase plasma concentrations of these drugs [see Clinical Pharmacology (12.3)].

Drugs Transported by P-gp

Concomitant use of ASPRUZYO Sprinkle and digoxin results in increased exposure to digoxin. The dose of digoxin may have to be adjusted [see Clinical Pharmacology (12.3)].

Drugs Metabolized by CYP2D6

The exposure to CYP2D6 substrates, such as tricyclic antidepressants and antipsychotics, may be increased during co-administration with ASPRUZYO Sprinkle, and lower doses of these drugs may be required.

Drugs Transported by OCT2

In subjects with type 2 diabetes mellitus, concomitant use of ASPRUZYO Sprinkle 1000 mg twice daily and metformin results in increased plasma levels of metformin. When ASPRUZYO Sprinkle 1000 mg twice daily is co-administered with metformin, metformin dose should not exceed 1700 mg/day. Monitor blood glucose levels and risks associated with high exposures of metformin.

Metformin exposure was not significantly increased when given with ranolazine 500 mg twice daily [see Clinical Pharmacology (12.3)].

8 USE IN SPECIFIC POPULATIONS

8.1 Pregnancy

Risk Summary

There are no available data on ranolazine use in pregnant women to inform any drug‑associated risks. Studies in rats and rabbits showed no evidence of fetal harm at exposures 4 times the maximum recommended human dose (MRHD) (see Data).

In the U.S. general population, the estimated background risk of major birth defects and of miscarriage of clinically recognized pregnancies is 2 to 4% and 15 to 20%, respectively.

Data

Animal Data

Embryofetal toxicity studies were conducted in rats and rabbits orally administered ranolazine during organogenesis. In rats, decreased fetal weight and reduced ossification were observed at doses (corresponding to 4-fold the AUC for the MRHD) that caused maternal weight loss. No adverse fetal effects were observed in either species exposed (AUC) to ranolazine at exposures (AUC) equal to the MRHD.

8.2 Lactation

Risk Summary

There are no data on the presence of ranolazine in human milk, the effects on the breastfed infant, or the effects on milk production. However, ranolazine is present in rat milk [see Use in Specific Populations (8.1)].The developmental and health benefits of breastfeeding should be considered along with the mother's clinical need for ranolazine and any potential adverse effects on the breastfed infant from ranolazine or from the underlying maternal condition.

Adult female rats were administered ranolazine orally from gestation day 6 through postnatal day 20. No adverse effects on pup development, behavior, or reproduction parameters were observed at a maternal dosage level of 60 mg/kg/day (equal to the MHRD based on AUC). At maternally toxic doses, male and female pups exhibited increased mortality and decreased body weight, and female pups showed increased motor activity. The pups were potentially exposed to low amounts of ranolazine via the maternal milk.

8.4 Pediatric Use

Safety and effectiveness have not been established in pediatric patients.

8.5 Geriatric Use

Of the chronic angina patients treated with ranolazine in controlled studies, 496 (48%) were ≥ 65 years of age, and 114 (11%) were ≥ 75 years of age. No overall differences in efficacy were observed between older and younger patients. There were no differences in safety for patients ≥ 65 years compared to younger patients, but patients ≥ 75 years of age on ranolazine, compared to placebo, had a higher incidence of adverse events, serious adverse events, and drug discontinuations due to adverse events. In general, dose selection for an elderly patient should usually start at the low end of the dosing range, reflecting the greater frequency of decreased hepatic, renal, or cardiac function, and of concomitant disease, or other drug therapy.

8.6 Use in Patients with Hepatic Impairment

ASPRUZYO Sprinkle is contraindicated in patients with liver cirrhosis. In a study of cirrhotic patients, the Cmaxof ranolazine was increased 30% in cirrhotic patients with mild (Child‑ Pugh Class A) hepatic impairment but increased 80% in cirrhotic patients with moderate (Child-Pugh Class B) hepatic impairment compared to patients without hepatic impairment. This increase was not enough to account for the 200% increase in QT prolongation seen in cirrhotic patients with mild to moderate hepatic impairment [see Clinical Pharmacology (12.2)].

8.7 Use in Patients with Renal Impairment

A pharmacokinetic study of ranolazine in subjects with severe renal impairment (CrCL< 30 mL/min) was stopped when 2 of 4 subjects developed acute renal failure after receiving ranolazine 500 mg twice daily for 5 days (lead-in phase) followed by 1000 mg twice a day (1 dose in one subject and 11 doses in the other). Increases in creatinine, BUN, and potassium were observed in 3 subjects during the 500 mg lead-in phase. One subject required hemodialysis, while the other 2 subjects improved upon drug discontinuation [see Warnings and Precautions (5.2)].Monitor renal function periodically in patients with moderate to severe renal impairment. Discontinue ASPRUZYO Sprinkle if acute renal failure develops.

In a separate study, Cmaxwas increased between 40% and 50% in patients with mild, moderate, or severe renal impairment compared to patients with no renal impairment, suggesting a similar increase in exposure in patients with renal failure independent of the degree of impairment. The pharmacokinetics of ranolazine has not been assessed in patients on dialysis.

10 OVERDOSAGE

Hypotension, QT prolongation, bradycardia, myoclonic activity, severe tremor, unsteady gait/incoordination, dizziness, nausea, vomiting, dysphasia, and hallucinations have been seen in cases of oral overdose of ranolazine. In cases of extreme overdose of ranolazine fatal outcomes have been reported. In clinical studies, high intravenous exposure resulted in diplopia, paresthesia, confusion, and syncope.

In addition to general supportive measures, continuous ECG monitoring may be warranted in the event of overdose.

Since ranolazine is about 62% bound to plasma proteins, hemodialysis is unlikely to be effective in clearing ranolazine.

11 DESCRIPTION

ASPRUZYO Sprinkle contains ranolazine, an antianginal available as white to off-white coated extended-release granules filled in a sachet for oral administration.

Ranolazine is a racemic mixture, chemically described as 1-piperazineacetamide, N‑(2,6-dimethylphenyl)-4-[2-hydroxy-3-(2-methoxyphenoxy)propyl]-(±)-. It has a molecular formula of C24H33N3O4, a molecular weight of 427.54 g/mole, and the following structural formula:

Ranolazine is off-white to white powder. Ranolazine is soluble in dichloromethane and methanol.

ASPRUZYO Sprinkle contains 500 mg or 1000 mg of ranolazine and the following inactive ingredients: amino methacrylate copolymer, dibutyl sebacate, ethyl cellulose, hypromellose, magnesium stearate, methacrylic acid and ethyl acrylate copolymer, microcrystalline cellulose, and talc.

12 CLINICAL PHARMACOLOGY

12.1 Mechanism of Action

The mechanism of action of ranolazine's antianginal effects has not been determined. Ranolazine has anti-ischemic and antianginal effects that do not depend upon reductions in heart rate or blood pressure. It does not affect the rate-pressure product, a measure of myocardial work, at maximal exercise. Ranolazine at therapeutic levels can inhibit the cardiac late sodium current (INa). However, the relationship of this inhibition to angina symptoms is uncertain.

The QT prolongation effect of ranolazine on the surface electrocardiogram is the result of inhibition of IKrwhich prolongs the ventricular action potential.

12.2 Pharmacodynamics

Hemodynamic Effects

Patients with chronic angina treated with ranolazine in controlled clinical studies had minimal changes in mean heart rate (< 2 bpm) and systolic blood pressure (< 3 mm Hg). Similar results were observed in subgroups of patients with CHF NYHA Class I or II, diabetes, or reactive airway disease, and in elderly patients.

Electrocardiographic Effects

Dose and plasma concentration-related increases in the QTcinterval [see Warnings and Precautions (5.1)],reductions in T wave amplitude, and, in some cases, notched T waves, have been observed in patients treated with ranolazine. These effects are believed to be caused by ranolazine and not by its metabolites. The relationship between the change in QTcand ranolazine plasma concentrations is linear, with a slope of about 2.6 msec/1000 ng/mL, through exposures corresponding to doses several-fold higher than the maximum recommended dose of 1000 mg twice daily. The variable blood levels attained after a given dose of ranolazine give a wide range of effects on QTc. At Tmaxfollowing repeat dosing at 1000 mg twice daily, the mean change in QTcis about 6 msec, but in the 5% of the population with the highest plasma concentrations, the prolongation of QTcis at least 15 msec. In cirrhotic subjects with mild or moderate hepatic impairment, the relationship between plasma level of ranolazine and QTcis much steeper [see Contraindications (4)].

Age, weight, gender, race, heart rate, congestive heart failure, diabetes, and renal impairment did not alter the slope of the QTc-concentration relationship of ranolazine.

No proarrhythmic effects were observed on 7-day Holter recordings in 3,162 acute coronary syndrome patients treated with ranolazine. There was a significantly lower incidence of arrhythmias (ventricular tachycardia, bradycardia, supraventricular tachycardia, and new atrial fibrillation) in patients treated with ranolazine (80%) versus placebo (87%), including ventricular tachycardia ≥ 3 beats (52% versus 61%). However, this difference in arrhythmias did not lead to a reduction in mortality, a reduction in arrhythmia hospitalization, or a reduction in arrhythmia symptoms.

12.3 Pharmacokinetics

The pharmacokinetic parameter of ranolazine after single dose administration of 1000 mg ASPRUZYO Sprinkle under fasting conditions are summarized in table 1.

Table 1: Pharmacokinetic parameters of ranolazine after single dose administration of 1000 mg ASPRUZYO Sprinkle under fasting conditions.

Parameter | ASPRUZYO Sprinkle
Parameter | Mean | CV (%)
Cmax(mcg/mL) | 1.95 | 30
Tmax(hr)* | 10 (2 to 16)
AUC0-t(mcg.hr/mL) | 31.4 | 36
AUC0-∞(mcg.hr/mL) | 31.7 | 36
T1/2(hr) | 5.3 | 27
Kel (hr^-1) | 0.15 | 29

*Median range (min-max) is provided

Ranolazine is extensively metabolized in the gut and liver and its absorption is highly variable. The pharmacokinetics of the (+) R-and (-) S-enantiomers of ranolazine are similar in healthy volunteers. Steady state is generally achieved within 3 days of twice-daily dosing with ranolazine. At steady state over the dose range of 500 to 1000 mg twice daily, Cmaxand AUC0-Tincrease slightly more than proportionally to dose, 120% and 140%, respectively. With twice-daily dosing, the trough:peak ratio of the ranolazine plasma concentration is 0.3 to 0.6. The pharmacokinetics of ranolazine is unaffected by age and sex.

Absorption and Distribution

After oral administration of ranolazine 1000 mg, median Tmaxwas 10 hours under fasting conditions and 4.5 to 6 hours under fed. After oral administration of^14C-ranolazine as a solution, 73% of the dose is systemically available as ranolazine or metabolites. The bioavailability of ranolazine from ranolazine granules relative to that from a solution of ranolazine is 76%. Because ranolazine is a substrate of P-gp, inhibitors of P-gp may increase the absorption of ranolazine. Over the concentration range of 0.25 to 10 mcg/mL, ranolazine is approximately 62% bound to human plasma proteins.

Food Effect

Compared to the fasted state, the systemic exposure (AUC) increased by 10% and peak drug concentration (Cmax) increased by 27% when the dose was given 30 minutes after a high fat meal. After administration with a low fat low calorie meal AUC increased by 6% and Cmaxincreased by 48%.

Metabolism and Excretion

Ranolazine is metabolized mainly by CYP3A and, to a lesser extent, by CYP2D6. Following a single oral dose of ranolazine solution, approximately 75% of the dose is excreted in urine and 25% in feces. Ranolazine is metabolized rapidly and extensively in the liver and intestine; less than 5% is excreted unchanged in urine and feces. The pharmacologic activity of the metabolites has not been well characterized. The mean elimination half-lives of ranolazine is approximately 5 hours post single dose ranging from 2 to 11 hours. After dosing to steady state with 500 mg to 1500 mg twice daily, the four most abundant metabolites in plasma have AUC values ranging from about 5 to 33% that of ranolazine and display apparent half-lives ranging from 6 to 22 hours.

Drug Interactions

Effect of Other Drugs on Ranolazine

In vitrodata indicate that ranolazine is a substrate of CYP3A and, to a lesser degree, of CYP2D6. Ranolazine is also a substrate of P-glycoprotein.

Strong CYP3A Inhibitors

Plasma levels of ranolazine with ranolazine 1000 mg twice daily are increased by 220% when co-administered with ketoconazole 200 mg twice daily [see Contraindications (4)].

Moderate CYP3A Inhibitors

Plasma levels of ranolazine with ranolazine 1000 mg twice daily are increased by 50 to 130% by diltiazem 180 to 360 mg, respectively. Plasma levels of ranolazine with ranolazine 750 mg twice daily are increased by 100% by verapamil 120 mg three times daily [see Drug Interactions (7.1)].

Weak CYP3A Inhibitors

The weak CYP3A inhibitors simvastatin (20 mg once daily) and cimetidine (400 mg three times daily) do not increase the exposure to ranolazine in healthy volunteers.

CYP3A Inducers

Rifampin 600 mg once daily decreases the plasma concentrations of ranolazine (1000 mg twice daily) by approximately 95% [see Contraindications (4)].

CYP2D6 Inhibitors

Paroxetine 20 mg once daily increased ranolazine concentrations by 20% in healthy volunteers receiving ranolazine 1000 mg twice daily. No dose adjustment of ranolazine is required in patients treated with CYP2D6 inhibitors.

Digoxin

Plasma concentrations of ranolazine are not significantly altered by concomitant digoxin at 0.125 mg once daily.

Effect of Ranolazine on Other Drugs

In vitroranolazine and its O-demethylated metabolite are weak inhibitors of CYP3A and moderate inhibitors of CYP2D6 and P-gp. In vitroranolazine is an inhibitor of OCT2.

CYP3A Substrates

The plasma levels of simvastatin, a CYP3A substrate, and its active metabolite are increased by 100% in healthy volunteers receiving 80 mg once daily and ranolazine 1000 mg twice daily [see Drug Interactions (7.2)].Mean exposure to atorvastatin (80 mg daily) is increased by 40% following co-administration with ranolazine (1000 mg twice daily) in healthy volunteers. However, in one subject the exposure to atorvastatin and metabolites was increased by ~400% in the presence of ranolazine.

Diltiazem

The pharmacokinetics of diltiazem is not affected by ranolazine in healthy volunteers receiving diltiazem 60 mg three times daily and ranolazine 1000 mg twice daily.

P-gp Substrates

Ranolazine increases digoxin concentrations by 50% in healthy volunteers receiving ranolazine 1000 mg twice daily and digoxin 0.125 mg once daily [see Drug Interactions (7.2)].

CYP2D6 Substrates

Ranolazine 750 mg twice daily increases the plasma concentrations of a single dose of immediate release metoprolol (100 mg), a CYP2D6 substrate, by 80% in extensive CYP2D6 metabolizers with no need for dose adjustment of metoprolol. In extensive metabolizers of dextromethorphan, a substrate of CYP2D6, ranolazine inhibits partially the formation of the main metabolite dextrorphan.

OCT2 Substrates

In subjects with type 2 diabetes mellitus, the exposure to metformin is increased by 40% and 80% following administration of ranolazine 500 and 1000 mg twice daily, respectively. If co-administered with ranolazine 1000 mg twice daily, do not exceed metformin doses of 1700 mg/day [see Drug Interactions (7.2)].

Alcohol

An in-vitrodissolution study was conducted to evaluate the impact of alcohol on extended-release characteristics of ASPRUZYO Sprinkle. The in-vitrostudy showed that alcohol causes a rapid release of ranolazine from ASPRUZYO Sprinkle that may increase the risk of adverse events associated with ASPRUZYO Sprinkle. Patients should not consume alcohol when taking ASPRUZYO Sprinkle.

13 NONCLINICAL TOXICOLOGY

13.1 Carcinogenesis, Mutagenesis, Impairment of Fertility

Ranolazine tested negative for genotoxic potential in the following assays: Ames bacterial mutation assay, Saccharomyces assay for mitotic gene conversion, chromosomal aberrations assay in Chinese hamster ovary (CHO) cells, mammalian CHO/HGPRT gene mutation assay, and mouse and rat bone marrow micronucleus assays.

There was no evidence of carcinogenic potential in mice or rats. The highest oral doses used in the carcinogenicity studies were 150 mg/kg/day for 21 months in rats (900 mg/m^2/day) and 50 mg/kg/day for 24 months in mice (150 mg/m^2/day). These maximally tolerated doses are 0.8 and 0.1 times, respectively, the daily maximum recommended human dose (MRHD) of 2,000 mg on a surface area basis. A published study reported that ranolazine promoted tumor formation and progression to malignancy when given to transgenic APC (min/+) mice at a dose of 30 mg/kg twice daily .The clinical significance of this finding is unclear.

In male and female rats, oral administration of ranolazine that produced exposures (AUC) approximately 3-fold or 5-fold higher, respectively, than the MRHD had no effect on fertility.

14 CLINICAL STUDIES

14.1 Chronic Stable Angina

CARISA (Combination Assessment of Ranolazine In Stable Angina) was a study in 823 chronic angina patients randomized to receive 12 weeks of treatment with twice-daily ranolazine 750 mg, 1000 mg, or placebo, who also continued on daily doses of atenolol 50 mg, amlodipine 5 mg, or diltiazem CD 180 mg. Sublingual nitrates were used in this study as needed.

In this trial, statistically significant (p < 0.05) increases in modified Bruce treadmill exercise duration and time to angina were observed for each ranolazine dose versus placebo, at both trough (12 hours after dosing) and peak (4 hours after dosing) plasma levels, with minimal effects on blood pressure and heart rate. The changes versus placebo in exercise parameters are presented in Table 2. Exercise treadmill results showed no increase in effect on exercise at the 1000 mg dose compared to the 750-mg dose.

Table 2 Exercise Treadmill Results (CARISA)

 | Mean Difference from Placebo (sec)
- Study | CARISA (N = 791)
- Ranolazine Twice-daily Dose | 750 mg | 1000 mg
- Exercise Duration - Trough - Peak | 24a; 34b | 24a; 26a
- Time to Angina - Trough - Peak | 30a; 38b | 26a; 38b
- Time to 1 mm ST-Segment - Depression - Trough - Peak | 20; 41b | 21; 35b

1. a p-value ≤ 0.05 b p-value ≤ 0.005

The effects of ranolazine on angina frequency and nitroglycerin use are shown in Table 3.

Table 3 Angina Frequency and Nitroglycerin Use (CARISA)

 |  | Placebo | Ranolazine 750 mga | Ranolazine 1000 mga
- Angina Frequency (attacks/week) | - N | 258 | 272 | 261
- Angina Frequency (attacks/week) | - Mean | 3.3 | 2.5 | 2.1
- Angina Frequency (attacks/week) | - P-valuevs placebo | - | 0.006 | <0.001
- Nitroglycerin Use - (doses/week) | - N | 252 | 262 | 244
- Nitroglycerin Use - (doses/week) | - Mean | 3.1 | 2.1 | 1.8
- Nitroglycerin Use - (doses/week) | - P-valuevs placebo | - | 0.016 | <0.001

1. a Twice daily

Tolerance to ranolazine did not develop after 12 weeks of therapy. Rebound increases in angina, as measured by exercise duration, have not been observed following abrupt discontinuation of ranolazine.

Ranolazine has been evaluated in patients with chronic angina who remained symptomatic despite treatment with the maximum dose of an antianginal agent. In the ERICA (Efficacy of Ranolazine In Chronic Angina) trial, 565 patients were randomized to receive an initial dose of ranolazine 500 mg twice daily or placebo for 1 week, followed by 6 weeks of treatment with ranolazine 1000 mg twice daily or placebo, in addition to concomitant treatment with amlodipine 10 mg once daily. In addition, 45% of the study population also received long-acting nitrates. Sublingual nitrates were used as needed to treat angina episodes. Results are shown in Table 4. Statistically significant decreases in angina attack frequency (p = 0.028) and nitroglycerin use (p = 0.014) were observed with ranolazine compared to placebo. These treatment effects appeared consistent across age and use of long-acting nitrates.

Table 4 Angina Frequency and Nitroglycerin Use (ERICA)

 |  | Placebo | Ranolazinea
Angina Frequency; (attacks/week) | - N | 281 | 277
Angina Frequency; (attacks/week) | - Mean | 4.3 | 3.3
Angina Frequency; (attacks/week) | - Median | 2.4 | 2.2
Nitroglycerin Use; (doses/week) | - N | 281 | 277
Nitroglycerin Use; (doses/week) | - Mean | 3.6 | 2.7
Nitroglycerin Use; (doses/week) | - Median | 1.7 | 1.3

1. a 1000 mg twice daily

Gender

Effects on angina frequency and exercise tolerance were considerably smaller in women than in men. In CARISA, the improvement in Exercise Tolerance Test (ETT) in females was about 33% of that in males at the 1000 mg twice-daily dose level. In ERICA, where the primary endpoint was angina attack frequency, the mean reduction in weekly angina attacks was 0.3 for females and 1.3 for males.

Race

There were insufficient numbers of non-Caucasian patients to allow for analyses of efficacy or safety by racial subgroup.

14.2 Lack of Benefit in Acute Coronary Syndrome

In a large (n = 6560) placebo-controlled trial (MERLIN-TIMI 36) in patients with acute coronary syndrome, there was no benefit shown on outcome measures. However, the study is somewhat reassuring regarding proarrhythmic risks, as ventricular arrhythmias were less common on ranolazine [see Clinical Pharmacology (12.2)],and there was no difference between ranolazine and placebo in the risk of all-cause mortality (relative risk ranolazine: placebo 0.99 with an upper 95% confidence limit of 1.22).

16 HOW SUPPLIED/STORAGE AND HANDLING

ASPRUZYO Sprinkle is supplied as white to off-white coated, extended-release granules in sachets of 500 or 1000 mg. Packages are

 | Strength | NDC
Unit-dose Sachet (Child-resistant) | 500 mg | NDC 47335-624-11
Unit-dose Sachet (Child-resistant) | 1000 mg | NDC 47335-625-11
30 Unit-dose Sachets (Child-resistant) | 500 mg | NDC 47335-624-30
30 Unit-dose Sachets (Child-resistant) | 1000 mg | NDC 47335-625-30
60 Unit-dose Sachets (Child-resistant) | 500 mg | NDC 47335-624-60
60 Unit-dose Sachets (Child-resistant) | 1000 mg | NDC 47335-625-60

Store ASPRUZYO Sprinkle at 20°C to 25°C (68°F to 77°F); excursions permitted between 15°C to 30°C (59°F to 86°F). [See USP Controlled Room Temperature].

17 PATIENT COUNSELING INFORMATION

Advise the patient to read the FDA-approved patient labeling (Patient Information).

Inform patients that ASPRUZYO Sprinkle will not abate an acute angina episode.

Drug Interactions

-
  -
    - Advise patients to discuss with their healthcare provider any prescription or over-the-counter medications and supplements prior to concomitant use [see Drug Interactions (7)].
    - Advise patients to limit grapefruit juice or grapefruit products when taking ASPRUZYO Sprinkle [see Drug Interactions (7)].

QT Interval Prolongation

-
  -
    - Advise patients to inform their physician of any personal or family history of QTcprolongation, congenital long QT syndrome, or if they are receiving drugs that prolong the QTcinterval such as [see Warnings and Precautions (5.1)].

Dizziness, Fainting

-
  -
    - Inform patients that ASPRUZYO Sprinkle may cause dizziness and lightheadedness. Patients should know how they react to ASPRUZYO Sprinkle before they operate an automobile or machinery, or engage in activities requiring mental alertness or coordination [see Adverse Reactions (6.1)].
    - Advise patients to contact their physician if they experience fainting spells while taking ASPRUZYO Sprinkle.

Administration

-
  -
    - Instruct patients to take ASPRUZYO Sprinkle as directed.
    - Advise patients not to crush or chew the granules.

All trademarks are the property of their respective owners.

Manufactured by:

Sun Pharmaceutical Industries Ltd.

Mohali, INDIA

Distributed by:

Sun Pharmaceutical Industries, Inc.

Cranbury, NJ 08512

FDA-04

Patient Medication Information

Patient Information

ASPRUZYO Sprinkle (as-PROO-zee-oh spring-KUHL)

(ranolazine) extended-release granules

What is ASPRUZYO Sprinkle?

ASPRUZYO Sprinkle is a prescription medicine used to treat angina that keeps coming back (chronic angina).

ASPRUZYO Sprinkle may be used with other medicines that are used for heart problems and blood pressure control.

It is not known if ASPRUZYO Sprinkle is safe and effective in children.

Do not take ASPRUZYO Sprinkle if:

- you take any of the following medicines:
- for fungus infection: ketoconazole, itraconazole
- for infection: clarithromycin
- for depression: nefazodone
- for HIV: nelfinavir, ritonavir, indinavir saquinavir
- for tuberculosis (TB): rifampin, rifabutin, rifapentine
- for seizures: phenobarbital, phenytoin, and carbamazepine
- St. John's wort
- you have scarring of your liver (liver cirrhosis)

Before taking ASPRUZYO Sprinkle, tell your healthcare provider about all of your medical conditions, including if you:

- have or have a family history of a heart problem, called 'QT prolongation' or 'long QT syndrome'
- have liver problems
- have kidney problems
- are pregnant or plan to become pregnant. It is not known if ASPRUZYO Sprinkle will harm your unborn baby.
- are breastfeeding or plan to breastfeed. It is not known if ranolazine passes into your breast milk. Talk to your healthcare provider about the best way to feed your baby.

Tell your healthcare provider about all the medicines you take,including prescription and over-the-counter medicines, vitamins, and herbal supplements. ASPRUZYO Sprinkle may affect the way other medicines work and other medicines may affect how ASPRUZYO Sprinkle works.

Know the medicines you take. Keep a list of them to show your healthcare provider or pharmacist when you get a new medicine.

How should I take ASPRUZYO Sprinkle?

- Take ASPRUZYO Sprinkle exactly as your healthcare provider tells you.
- Your healthcare provider will tell you how much ASPRUZYO Sprinkle to take and when to take it. Do not change your dose unless your healthcare provider tells you to.
- Tell your healthcare provider if you still have symptoms of angina after starting ASPRUZYO Sprinkle.
- Take ASPRUZYO Sprinkle 2 times a day.
- ASPRUZYO Sprinkle may be taken or given as follows:

To open the sachet fold back on dotted line and tear at notch or use scissors.

Directions for use with soft food (e.g., applesauce and yogurt):

- Sprinkle granules on one tablespoonful of soft food and consume immediately.
- Do not crush or chew the granules.

Giving ASPRUZYO Sprinkle with water through a 12 French or larger nasogastric (NG) tube:

- Add the granules from the sachet to a plastic catheter tip syringe and add 50 mL of water.
- Gently shake the syringe for about 15 seconds.
- Connect the catheter tip syringe to the NG tube and give the mixture right away.
- Make sure that no granules are left in the syringe. Rinse the syringe with about 15 mL of additional water if needed and give through NG tube.

Giving ASPRUZYO Sprinkle with water through a 12 French or larger gastric (G) tube:

- Add the granules from the sachet to a plastic catheter tip syringe and add 30 mL of water.
- Gently shake the syringe for about 15 seconds.
- Connect the catheter tip syringe to the G-tube and give the mixture right away.
- Rinse the syringe with 20 mL of additional water and give through G-tube.
- Make sure that no granules are left in the syringe. Rinse the syringe with about 15 mL of additional water if needed and give through G-tube.
- If you miss a dose of ASPRUZYO Sprinkle, take the next dose of ASPRUZYO Sprinkle at your regular time. Do not make up for the missed dose. Do not take 2 doses at the same time.
- If you take too much ASPRUZYO Sprinkle, call your healthcare provider, or go to the nearest emergency room right away.

What should I avoid while taking ASPRUZYO Sprinkle?

- You should limit grapefruit, grapefruit juice, and products that contain grapefruit during treatment with ASPRUZYO Sprinkle. Grapefruit products can increase the amount of ASPRUZYO Sprinkle in your body.
- ASPRUZYO Sprinkle can cause dizziness, lightheadedness, and fainting. If you have these symptoms, do not drive a car, use machinery, or do anything that needs you to be alert.
- You should not drink alcohol during treatment with ASPRUZYO Sprinkle.

What are the possible side effects of ASPRUZYO Sprinkle?

ASPRUZYO Sprinkle may cause serious side effects, including:

- Changes in the electrical activity of your heart called QT prolongation. Your healthcare provider may check the electrical activity of your heart with an electrocardiogram (ECG). Tell your healthcare provider right away if you feel faint, lightheaded, or feel your heart beating irregularly or fast during treatment with ASPRUZYO Sprinkle. These may be symptoms related to QT prolongation.
- Kidney failure in people who already have severe kidney problems. Your healthcare provider may do blood tests to check your kidneys during treatment with ASPRUZYO Sprinkle.

The most common side effects of ASPRUZYO Sprinkle include:

- dizziness
- headache
- constipation
- nausea

These are not all of the possible side effects of ASPRUZYO Sprinkle.

Call your healthcare provider for medical advice about side effects. You may report side effects to FDA at 1-800-FDA-1088.

How should I store ASPRUZYO Sprinkle?

- Store ASPRUZYO Sprinkle at room temperature between 68°F to 77°F (20°C to 25°C).
- Keep ASPRUZYO Sprinkle and all medicines out of the reach of children.

General information about the safe and effective use of ASPRUZYO Sprinkle.

Medicines are sometimes prescribed for purposes other than those listed in a Patient Information leaflet. Do not use ASPRUZYO Sprinkle for a condition for which it was not prescribed. Do not give ASPRUZYO Sprinkle to other people, even if they have the same condition you have. It may harm them. You can ask your pharmacist or healthcare provider for information about ASPRUZYO Sprinkle that is written for health professionals.

What are the ingredients in ASPRUZYO Sprinkle?

Active ingredient:ranolazine

Inactive ingredients:amino methacrylate copolymer, dibutyl sebacate, ethyl cellulose, hypromellose, magnesium stearate, methacrylic acid and ethyl acrylate copolymer, microcrystalline cellulose, and talc.

Manufactured by:Sun Pharmaceutical Industries Ltd., Mohali, INDIA

Distributed by:Sun Pharmaceutical Industries, Inc., Cranbury, NJ 08512

For more information, call 1-800-818-4555.

1. This Patient Information has been approved by the U.S. Food and Drug Administration. Issued: February/2022

Package/Label Display Panel

NDC 47335-624-30

ASPRUZYO Sprinkle™ (ranolazine) extended-release granules

500 mg per sachet

1. Rx only SUN PHARMA

Contains 30 sachets

Package/Label Display Panel

NDC 47335-624-60

ASPRUZYO Sprinkle™ (ranolazine) extended-release granules

500 mg per sachet

1. Rx only SUN PHARMA

Contains 60 sachets

Package/Label Display Panel

NDC 47335-624-11

ASPRUZYO Sprinkle™ (ranolazine) extended-release granules

500 mg per sachet

- Each sachet contains 500 mg ranolazine
- Recommended Dosage: See prescribing information.

1. Rx only SUN PHARMA
2. This package is child-resistant.
3. Keep out of reach of children.